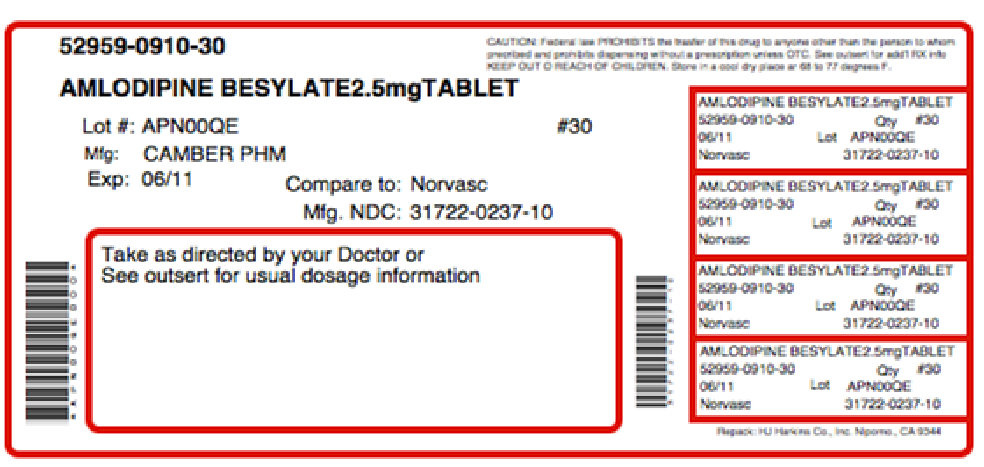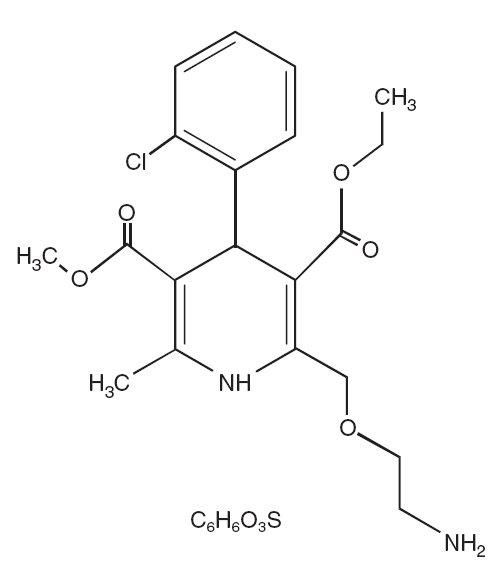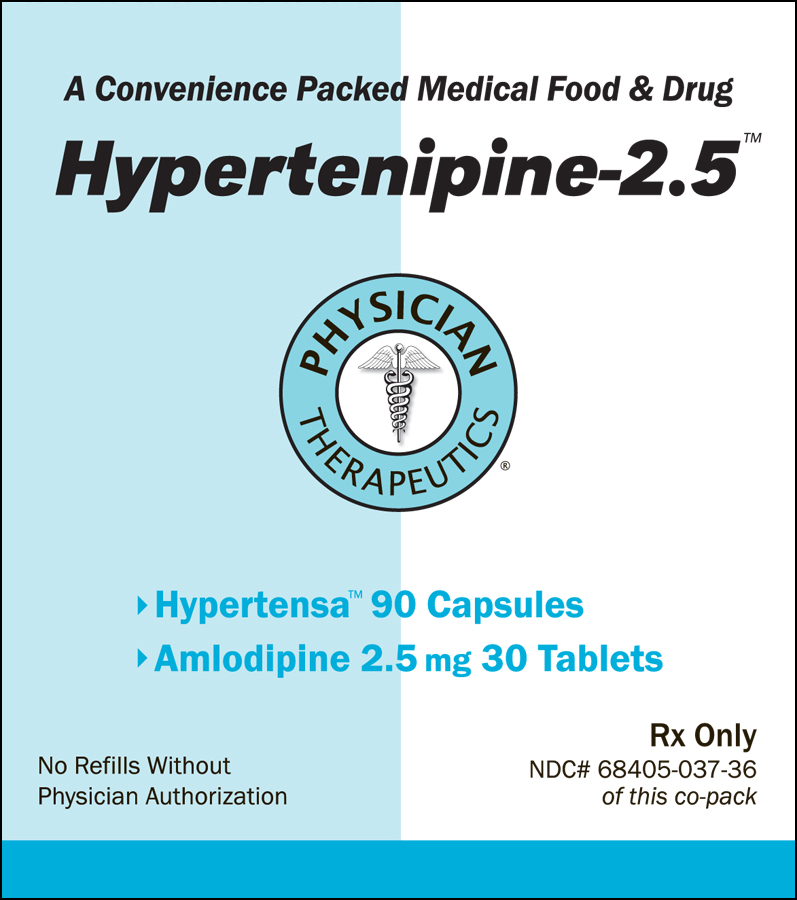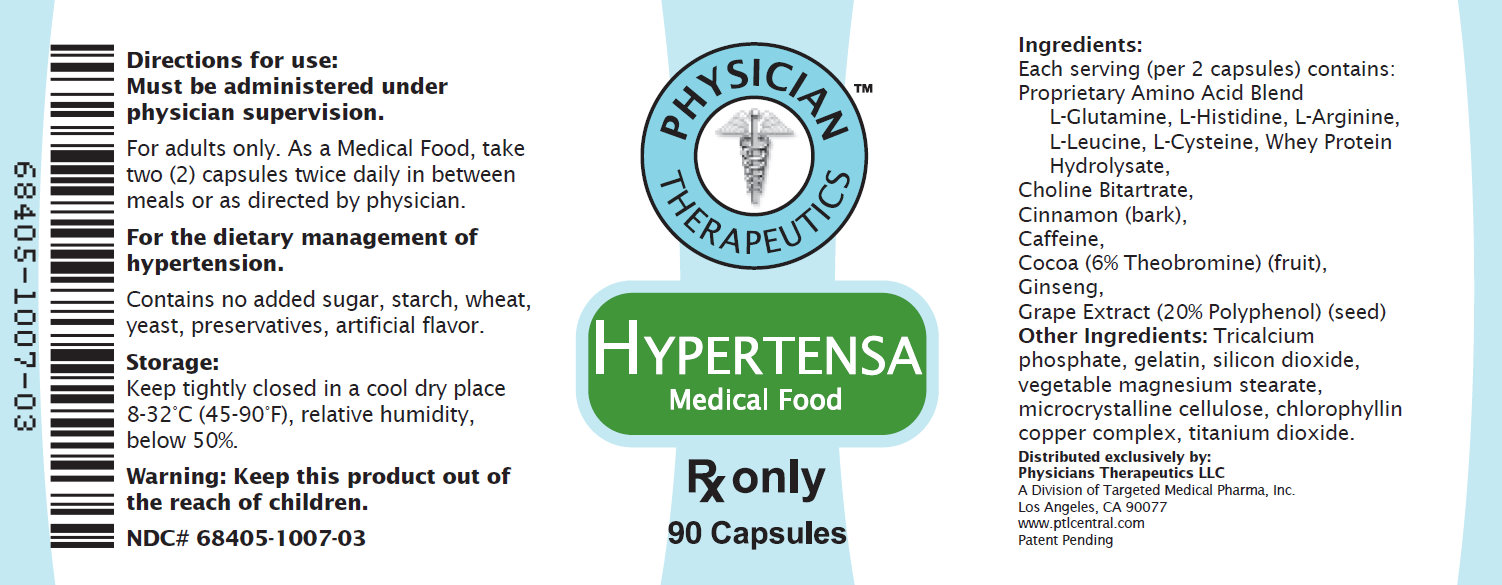 DRUG LABEL: Hypertenipine
NDC: 68405-037 | Form: KIT | Route: ORAL
Manufacturer: Physician Therapeutics LLC
Category: prescription | Type: HUMAN PRESCRIPTION DRUG LABEL
Date: 20110801

ACTIVE INGREDIENTS: AMLODIPINE BESYLATE 2.5 mg/1 1; ARGININE 90 mg/1 1
INACTIVE INGREDIENTS: CELLULOSE, MICROCRYSTALLINE; ANHYDROUS DIBASIC CALCIUM PHOSPHATE; MAGNESIUM STEARATE; MAGNESIUM STEARATE; CELLULOSE, MICROCRYSTALLINE; MALTODEXTRIN; GELATIN

Hypertenipine-2.5

DESCRIPTION
Amlodipine besylate, USP is a long-acting calcium channel blocker.
Amlodipine besylate, USP is chemically described as 3-Ethyl-5-methyl (±)-2-[(2-aminoethoxy) methy l ] - 4 - (2 - c h l o r o p h e ny l) - 1 , 4 - d i hydro-6-methy l - 3 , 5 - py r i d i n e d i c a r b ox y l a t e, monobenzenesulphonate. Its molecular formula is C20H25CIN2O5•C6H6O3S, and its structural formula is:
Amlodipine besylate, USP is a white crystalline powder with a molecular weight of 567.1. It is slightly soluble in water and sparingly soluble in ethanol. Amlodipine besylate tablets are formulated as white tablets equivalent to 2.5, 5 and 10 mg of amlodipine for oral administration. In addition to the active ingredient, amlodipine besylate, USP, each tablet contains the following inactive ingredients: microcrystalline cellulose, dibasic calcium phosphate anhydrous, sodium starch glycolate, and magnesium stearate.

CLINICAL PHARMACOLOGY
Mechanism of Action
Amlodipine is a dihydropyridine calcium antagonist (calcium ion antagonist or slow-channel blocker)
that inhibits the transmembrane influx of calcium ions into vascular smooth muscle and cardiac
muscle. Experimental data suggest that amlodipine binds to both dihydropyridine and
nondihydropyridine binding sites. The contractile processes of cardiac muscle and vascular smooth
muscle are dependent upon the movement of extracellular calcium ions into these cells through
specific ion channels. Amlodipine inhibits calcium ion influx across cell membranes selectively, with
a greater effect on vascular smooth muscle cells than on cardiac muscle cells. Negative inotropic
effects can be detected in vitrobut such effects have not been seen in intact animals at therapeutic
doses. Serum calcium concentration is not affected by amlodipine. Within the physiologic pH range,
amlodipine is an ionized compound (pKa=8.6), and its kinetic interaction with the calcium channel
receptor is characterized by a gradual rate of association and dissociation with the receptor binding
site, resulting in a gradual onset of effect.
Amlodipine is a peripheral arterial vasodilator that acts directly on vascular smooth muscle to cause
a reduction in peripheral vascular resistance and reduction in blood pressure.
The precise mechanisms by which amlodipine relieves angina have not been fully delineated, but
are thought to include the following:
Exertional Angina: In patients with exertional angina, amlodipine besylate reduces the total
peripheral resistance (afterload) against which the heart works and reduces the rate pressure
product, and thus myocardial oxygen demand, at any given level of exercise.
Vasospastic Angina: Amlodipine besylate has been demonstrated to block constriction and restore
blood flow in coronary arteries and arterioles in response to calcium, potassium epinephrine,
serotonin, and thromboxane A2 analog in experimental animal models and in human coronary
vessels in vitro. This inhibition of coronary spasm is responsible for the effectiveness of amlodipine
besylate in vasospastic (Prinzmetal’s or variant) angina.

Pharmacokinetics and Metabolism
After oral administration of therapeutic doses of amlodipine besylate, absorption produces peak
plasma concentrations between 6 and 12 hours. Absolute bioavailability has been estimated to be
between 64 and 90%. The bioavailability of amlodipine besylate is not altered by the presence of
food.
Amlodipine is extensively (about 90%) converted to inactive metabolites via hepatic metabolism with
10% of the parent compound and 60% of the metabolites excreted in the urine. Ex vivostudies have
shown that approximately 93% of the circulating drug is bound to plasma proteins in hypertensive
patients. Elimination from the plasma is biphasic with a terminal elimination half-life of about 30-50
hours. Steady-state plasma levels of amlodipine are reached after 7 to 8 days of consecutive daily
dosing.
The pharmacokinetics of amlodipine are not significantly influenced by renal impairment. Patients
with renal failure may therefore receive the usual initial dose.
Elderly patients and patients with hepatic insufficiency have decreased clearance of amlodipine with
a resulting increase in AUC of approximately 40-60%, and a lower initial dose may be required. A
similar increase in AUC was observed in patients with moderate to severe heart failure.
Pediatric Patients
Sixty-two hypertensive patients aged 6 to 17 years received doses of amlodipine besylate between
1.25 mg and 20 mg.Weight-adjusted clearance and volume of distribution were similar to values in
adults.

Pharmacodynamics
Hemodynamics Following administration of therapeutic doses to patients with hypertension,
amlodipine besylate produces vasodilation resulting in a reduction of supine and standing blood
pressures. These decreases in blood pressure are not accompanied by a significant change in heart
rate or plasma catecholamine levels with chronic dosing. Although the acute intravenous
administration of amlodipine decreases arterial blood pressure and increases heart rate in
hemodynamic studies of patients with chronic stable angina, chronic oral administration of
amlodipine in clinical trials did not lead to clinically significant changes in heart rate or blood
pressures in normotensive patients with angina.
With chronic once daily oral administration, antihypertensive effectiveness is maintained for at least
24 hours. Plasma concentrations correlate with effect in both young and elderly patients. The
magnitude of reduction in blood pressure with amlodipine besylate is also correlated with the height
of pretreatment elevation; thus, individuals with moderate hypertension (diastolic pressure 105-114
mmHg) had about a 50% greater response than patients with mild hypertension (diastolic pressure
90-104 mmHg). Normotensive subjects experienced no clinically significant change in blood
pressures (+1/–2 mmHg).
In hypertensive patients with normal renal function, therapeutic doses of amlodipine besylate
resulted in a decrease in renal vascular resistance and an increase in glomerular filtration rate and
effective renal plasma flow without change in filtration fraction or proteinuria.
As with other calcium channel blockers, hemodynamic measurements of cardiac function at rest and
during exercise (or pacing) in patients with normal ventricular function treated with amlodipine
besylate have generally demonstrated a small increase in cardiac index without significant influence
on dP/dt or on left ventricular end diastolic pressure or volume. In hemodynamic studies, amlodipine
besylate has not been associated with a negative inotropic effect when administered in the
therapeutic dose range to intact animals and man, even when co-administered with beta-blockers to
man. Similar findings, however, have been observed in normals or well-compensated patients with
heart failure with agents possessing significant negative inotropic effects.
Electrophysiologic Effects: Amlodipine besylate does not change sinoatrial nodal function or
atrioventricular conduction in intact animals or man. In patients with chronic stable angina,
intravenous administration of 10 mg did not significantly alter A-H and H-V conduction and sinus
node recovery time after pacing. Similar results were obtained in patients receiving amlodipine
besylate and concomitant beta blockers. In clinical studies in which amlodipine besylate was
administered in combination with beta-blockers to patients with either hypertension or angina, no
adverse effects on electrocardiographic parameters were observed. In clinical trials with angina
patients alone, amlodipine besylate therapy did not alter electrocardiographic intervals or produce
higher degrees of AV blocks.

Clinical Studies
Effects in Hypertension
Adult Patients: The antihypertensive efficacy of amlodipine besylate has been demonstrated in a
total of 15 double-blind, placebo-controlled, randomized studies involving 800 patients on amlodipine
besylate and 538 on placebo. Once daily administration produced statistically significant placebocorrected
reductions in supine and standing blood pressures at 24 hours postdose, averaging about
12/6 mmHg in the standing position and 13/7 mmHg in the supine position in patients with mild to
moderate hypertension. Maintenance of the blood pressure effect over the 24-hour dosing interval
was observed, with little difference in peak and trough effect. Tolerance was not demonstrated in
patients studied for up to 1 year. The 3 parallel, fixed dose, dose response studies showed that the
reduction in supine and standing blood pressures was dose-related within the recommended dosing
range. Effects on diastolic pressure were similar in young and older patients. The effect on systolic
pressure was greater in older patients, perhaps because of greater baseline systolic pressure.
Effects were similar in black patients and in white patients.
Pediatric Patients: Two-hundred sixty-eight hypertensive patients aged 6 to 17 years were
randomized first to amlodipine besylate 2.5 or 5 mg once daily for 4 weeks and then randomized
again to the same dose or to placebo for another 4 weeks. Patients receiving 5 mg at the end of 8
weeks had lower blood pressure than those secondarily randomized to placebo. The magnitude of
the treatment effect is difficult to interpret, but it is probably less than 5 mmHg systolic on the 5 mg
dose. Adverse events were similar to those seen in adults.
Effects in Chronic Stable Angina:
The effectiveness of 5 to 10 mg/day of amlodipine besylate in exercise-induced angina has been
evaluated in 8 placebo-controlled, double-blind clinical trials of up to 6 weeks duration involving 1038
patients (684 amlodipine besylate, 354 placebo) with chronic stable angina. In 5 of the 8 studies
significant increases in exercise time (bicycle or treadmill) were seen with the 10 mg dose. Increases
in symptom-limited exercise time averaged 12.8% (63 sec) for amlodipine besylate 10 mg, and
averaged 7.9% (38 sec) for amlodipine besylate 5 mg. Amlodipine besylate 10 mg also increased
time to 1 mm ST segment deviation in several studies and decreased angina attack rate. The
sustained efficacy of amlodipine besylate in angina patients has been demonstrated over long-term
dosing. In patients with angina there were no clinically significant reductions in blood pressures (4/1
mmHg) or changes in heart rate (+0.3 bpm).
Effects in Vasospastic Angina:
In a double-blind, placebo-controlled clinical trial of 4 weeks duration in 50 patients, amlodipine
besylate therapy decreased attacks by approximately 4/week compared with a placebo decrease of
approximately 1/week (p less than 0.01). Two of 23 amlodipine besylate and 7 of 27 placebo patients
discontinued from the study due to lack of clinical improvement.
Studies in Patients with Congestive Heart Failure:
Amlodipine besylate has been compared to placebo in four 8-12 week studies of patients with NYHA
class II/III heart failure, involving a total of 697 patients. In these studies, there was no evidence of
worsened heart failure based on measures of exercise tolerance, NYHA classification, symptoms,
or left ventricular ejection fraction. In a long-term (follow-up at least 6 months, mean 13.8 months)
placebo-controlled mortality/morbidity study of amlodipine besylate 5 to 10 mg in 1153 patients with
NYHA classes III (n=93 1) or IV (n=222) heart failure on stable doses of diuretics, digoxin, and ACE
inhibitors, amlodipine besylate had no effect on the primary endpoint of the study which was the
combined endpoint of all-cause mortality and cardiac morbidity (as defined by life-threatening
arrhythmia, acute myocardial infarction, or hospitalization for worsened heart failure), or on NYHA
classification, or symptoms of heart failure. Total combined all-cause mortality and cardiac morbidity
events were 222/571 (39%) for patients on amlodipine besylate and 246/583 (42%) for patients on
placebo; the cardiac morbid events represented about 25% of the endpoints in the study.
Another study (PRAISE-2) randomized patients with NYHA class III (80%) or IV (20%) heart failure
without clinical symptoms or objective evidence of underlying ischemic disease, on stable doses of
ACE inhibitor (99%), digitalis (99%) and diuretics (99%), to placebo (n=827) or amlodipine besylate
(n=827) and followed them for a mean of 33 months. There was no statistically significant difference
between amlodipine besylate and placebo in the primary endpoint of all cause mortality (95%
confidence limits from 8% reduction to 29% increase on amlodipine besylate). With amlodipine
besylate there were more reports of pulmonary edema.

INDICATIONS AND USAGE
1. Hypertension
Amlodipine besylate is indicated for the treatment of hypertension. It may be used alone or in
combination with other antihypertensive agents.
2. Coronary Artery Disease
Cronic Stable Angina
Amlodipine besylate is indicated for the symptomatic treatment of chronic stable angina.
Amlodipine besylate may be used alone or in combination with other antianginal agents.
Vasospastic Angina (Prinzmetal’s or Variant Angina)
Amlodipine besylate is indicated for the treatment of confirmed or suspected vasospastic angina.
Amlodipine besylate may be used as monotherapy or in combination with other antianginal drugs.

CONTRAINDICATIONS
Amlodipine besylate is contraindicated in patients with known sensitivity to amlodipine.

WARNINGS
Increased Angina and/or Myocardial Infarction: Rarely, patients, particularly those with severe
obstructive coronary artery disease, have developed documented increased frequency, duration
and/or severity of angina or acute myocardial infarction on starting calcium channel blocker therapy
or at the time of dosage increase. The mechanism of this effect has not been elucidated.

PRECAUTIONS
General: Since the vasodilation induced by amlodipine besylate is gradual in onset, acute
hypotension has rarely been reported after oral administration. Nonetheless, caution as with any
other peripheral vasodilator, should be exercised when administering amlodipine besylate,
particularly in patients with severe aortic stenosis.
Use in Patients with Congestive Heart Failure: In general, calcium channel blockers should be
used with caution in patients with heart failure. Amlodipine besylate (5 to 10 mg per day) has been
studied in a placebo-controlled trial of 1153 patients with NYHA Class III or IV heart failure (see
CLINICAL PHARMACOLOGY) on stable doses of ACE inhibitor, digoxin, and diuretics. Follow-up
was at least 6 months, with a mean of about 14 months. There was no overall adverse effect on
survival or cardiac morbidity (as defined by life-threatening arrhythmia, acute myocardial infarction,
or hospitalization for worsened heart failure). Amlodipine besylate has been compared to placebo in
four 8-12 week studies of patients with NYHA class II/III heart failure, involving a total of 697 patients.
In these studies, there was no evidence of worsened heart failure based on measures of exercise
tolerance, NYHA classification, symptoms, or LVEF.
Beta-Blocker Withdrawal: Amlodipine besylate is not a beta-blocker and therefore gives no
protection against the dangers of abrupt beta-blocker withdrawal; any such withdrawal should be by
gradual reduction of the dose of beta-blocker.
Patients with Hepatic Failure: Since amlodipine besylate is extensively metabolized by the liver
and the plasma elimination half-life (t 1/2) is 56 hours in patients with impaired hepatic function,
caution should be exercised when administering amlodipine besylate to patients with severe hepatic
impairment.

DRUG INTERACTIONS

Drug Interactions: In vitro data indicate that amlodipine besylate has no effect on the human
plasma protein binding of digoxin, phenytoin, warfarin, and indomethacin.
Effect of other agents on Amlodipine besylate.
CIMETIDINE: Co-administration of amlodipine besylate with cimetidine did not alter the
pharmacokinetics of amlodipine besylate.
GRAPEFRUIT JUICE: Co-administration of 240 mL of grapefruit juice with a single oral dose of
amlodipine 10 mg in 20 healthy volunteers had no significant effect on the C6H6O3S
pharmacokinetics of amlodipine.
MAALOX (antacid): Co-administration of the antacid Maalox with a single dose of amlodipine
besylate had no significant effect on the pharmacokinetics of amlodipine besylate.
SILDENAFIL: A single 100 mg dose of sildenafil (Viagra®) in subjects with essential hypertension
had no effect on the pharmacokinetic parameters of amlodipine besylate. When amlodipine besylate
and sildenafil were used in combination, each agent independently exerted its own blood pressure
lowering effect.
Effect of Amlodipine besylate on other agents.
ATORVASTATIN: Co-administration of multiple 10 mg doses of amlodipine besylate with 80 mg of
atorvastatin resulted in no significant change in the steady state pharmacokinetic parameters of
atorvastatin.
DIGOXIN: Co-administration of amlodipine besylate with digoxin did not change serum digoxin levels
or digoxin renal clearance in normal volunteers.
ETHANOL (alcohol): Single and multiple 10 mg doses of amlodipine besylate had no significant
effect on the pharmacokinetics of ethanol.
WARFARIN: Co-administration of amlodipine besylate with warfarin did not change the warfarin
prothrombin response time.
In clinical trials, amlodipine besylate has been safely administered with thiazide diuretics, betablockers,
angiotensin-converting enzyme inhibitors, long-acting nitrates, sublingual nitroglycerin,
digoxin, warfarin, non-steroidal anti-inflammatory drugs, antibiotics, and oral hypoglycemic drugs.

Drug/Laboratory Test Interactions: None known.

CARCINOGENESIS AND MUTAGENESIS AND IMPAIRMENT OF FERTILITY

Carcinogenesis, Mutagenesis, Impairment of Fertility: Rats and mice treated with amlodipine
maleate in the diet for up to two years, at concentrations calculated to provide daily dosage levels of
0.5, 1.25, and 2.5 amlodipine mg/kg/day showed no evidence of a carcinogenic effect of the drug.
For the mouse, the highest dose was, on a mg/m2 basis, similar to the maximum recommended
human dose of 10 mg amlodipine/day*). For the rat, the highest dose, was on a mg/m2 basis, about
twice the maximum recommended human dose*.
Mutagenicity studies conducted with amlodipine maleate revealed no drug related effects at either
the gene or chromosome level.
There was no effect on the fertility of rats treated orally with amlodipine maleate (males for 64 days
and females for 14 days prior to mating) at doses up to 10 mg amlodipine/kg/day (8 times* the
maximum recommended human dose of 10 mg/day on a mg/m2 basis).

PREGNANCY

Pregnancy Category C: No evidence of teratogenicity or other embryo/fetal toxicity was found when
pregnant rats and rabbits were treated orally with amlodipine maleate at doses up to 10 mg
amlodipine/kg/day (respectively 8 times* and 23 times* the maximum recommended human dose of
10 mg on a mg/m2 basis) during their respective periods of major organogenesis. However, litter size
was significantly decreased (by about 50%) and the number of intrauterine deaths was significantly
increased (about 5-fold) in rats receiving amlodipine maleate at a dose equivalent to 10 mg
amlodipine/kg/day for 14 days before mating and throughout mating and gestation. Amlodipine
maleate has been shown to prolong both the gestation period and the duration of labor in rats at this
dose. There are no adequate and well-controlled studies in pregnant women. Amlodipine should be
used during pregnancy only if the potential benefit justifies the potential risk to the fetus.
*Based on patient weight of 50 kg.

NURSING MOTHERS

Nursing Mothers: It is not known whether amlodipine is excreted in human milk. In the absence of
this information, it is recommended that nursing be discontinued while amlodipine besylate is
administered.

PEDIATRIC USE

Pediatric Use: The effect of amlodipine besylate on blood pressure in patients less than 6 years of
age is not known.

GERIATRIC USE

Geriatric Use: Clinical studies of amlodipine besylate did not include sufficient numbers of subjects
aged 65 and over to determine whether they respond differently from younger subjects. Other
reported clinical experience has not identified differences in responses between the elderly and
younger patients. In general, dose selection for an elderly patient should be cautious, usually starting
at the low end of the dosing range, reflecting the greater frequency of decreased hepatic, renal, or
cardiac function, and of concomitant disease or other drug therapy. Elderly patients have decreased
clearance of amlodipine with a resulting increase of AUC of approximately 40-60%, and a lower
initial dose may be required (see DOSAGE AND ADMINISTRATION).

ADVERSE REACTIONS
Amlodipine besylate has been evaluated for safety in more than 11,000 patients in U.S. and foreign
clinical trials. In general, treatment with amlodipine besylate was well-tolerated at doses up to 10 mg
daily. Most adverse reactions reported during therapy with amlodipine besylate were of mild or
moderate severity. In controlled clinical trials directly comparing amlodipine besylate (N=1730) in
doses up to 10 mg to placebo (N=1250), discontinuation of amlodipine besylate due to adverse
reactions was required in only about 1.5% of patients and was not significantly different from placebo
(about 1%). The most common side effects are headache and edema. The incidence (%) of side
effects which occurred in a dose related manner are as follows:

Adverse Event | 2.5 mg N=275 | 5 mg N=296 | 10 mg N=268 | Placebo N=520
Edema | 1.8 | 3 | 10.8 | 0.6
Dizziness | 1.1 | 3.4 | 3.4 | 1.5
Flushing | 0.7 | 1.4 | 2.6 | 0
Palpitation | 0.7 | 1.4 | 4.5 | 0.6

Other adverse experiences which were not clearly dose related but which were reported with an
incidence greater than 1% in placebo-controlled clinical trials include the following:

Placebo-Controlled Studies | AMLODIPINE BESYLATE (%) (N=1730) | PLACEBO (%) (N=1250)
Headache | 7.3 | 7.8
Fatigue | 4.5 | 2.8
Nausea | 2.9 | 1.9
Abdominal Pain | 1.6 | 0.3
Somnolence | 1.4 | 0.6

For several adverse experiences that appear to be drug and dose related, there was a greater
incidence in women than men associated with amlodipine treatment as shown in the following table:

 |  | AMLODIPINE BESYLATE |  | PLACEBO
Adverse Event | Male=% (N=1218) | Female=% (N=512) | Male=% (N=914) | Female=% (N=336)
Edema | 5.6 | 14.6 | 1.4 | 5.1
Flushing | 1.5 | 4.5 | 0.3 | 0.9
Palpitations | 1.4 | 3.3 | 0.9 | 0.9
Somnolence | 1.3 | 1.6 | 0.8 | 0.3

The following events occurred in less than 1% but greater than 0.1% of patients in controlled clinical trials or under
conditions of open trials or marketing experience where a causal relationship is uncertain; they are
listed to alert the physician to a possible relationship:
Cardiovascular: arrhythmia (including ventricular tachycardia and atrial fibrillation), bradycardia,
chest pain, hypotension, peripheral ischemia, syncope, tachycardia, postural dizziness, postural
hypotension, vasculitis.
Central and Peripheral Nervous System: hypoesthesia, neuropathy peripheral, paresthesia,
tremor, vertigo.
Gastrointestinal: anorexia, constipation, dyspepsia,** dysphagia, diarrhea, flatulence, pancreatitis,
vomiting, gingival hyperplasia.
General: allergic reaction, asthenia,** back pain, hot flushes, malaise, pain, rigors, weight gain,
weight decrease.
Musculoskeletal System: arthralgia, arthrosis, muscle cramps,** myalgia.
Psychiatric: sexual dysfunction (male** and female), insomnia, nervousness, depression, abnormal
dreams, anxiety, depersonalization.
Respiratory System: dyspnea, * * epistaxis.
Skin and Appendages: angioedema, erythema multiforme, pruritus,** rash,** rash erythematous,
rash maculopapular.
* * These events occurred in less than 1% in placebo-controlled trials, but the incidence of these side
effects was between 1% and 2% in all multiple dose studies.
Special Senses: abnormal vision, conjunctivitis, diplopia, eye pain, tinnitus.
Urinary System: micturition frequency, micturition disorder, nocturia.
Autonomic Nervous System: dry mouth, sweating increased.
Metabolic and Nutritional: hyperglycemia, thirst.
Hemopoietic: leukopenia, purpura, thrombocytopenia.
The following events occurred in less than 0.1% of patients: cardiac failure, pulse irregularity, extrasystoles,
skin discoloration, urticaria, skin dryness, alopecia, dermatitis, muscle weakness, twitching, ataxia,
hypertonia, migraine, cold and clammy skin, apathy, agitation, amnesia, gastritis, increased appetite,
loose stools, coughing, rhinitis, dysuria, polyuria, parosmia, taste perversion, abnormal visual
accommodation, and xerophthalmia.
Other reactions occurred sporadically and cannot be distinguished from medications or concurrent
disease states such as myocardial infarction and angina.
Amlodipine besylate therapy has not been associated with clinically significant changes in routine
laboratory tests. No clinically relevant changes were noted in serum potassium, serum glucose, total
triglycerides, total cholesterol, HDL cholesterol, uric acid, blood urea nitrogen, or creatinine.
The following postmarketing event has been reported infrequently where a causal relationship is
uncertain: gynecomastia. In postmarketing experience, jaundice and hepatic enzyme elevations
(mostly consistent with cholestasis or hepatitis) in some cases severe enough to require
hospitalization have been reported in association with use of amlodipine.
Amlodipine besylate has been used safely in patients with chronic obstructive pulmonary disease,
well-compensated congestive heart failure, coronary artery disease, peripheral vascular disease,
diabetes mellitus, and abnormal lipid profiles.

OVERDOSAGE
Single oral doses of amlodipine maleate equivalent to 40 mg amlodipine/kg and 100 mg
amlodipine/kg in mice and rats, respectively, caused deaths. Single oral amlodipine maleate doses
equivalent to 4 or more mg amlodipine/kg or higher in dogs (11 or more times the maximum
recommended human dose on a mg/m2 basis) caused a marked peripheral vasodilation and
hypotension.
Overdosage might be expected to cause excessive peripheral vasodilation with marked hypotension
and possibly a reflex tachycardia. In humans, experience with intentional overdosage of amlodipine
besylate is limited. Reports of intentional overdosage include a patient who ingested 250 mg and
was asymptomatic and was not hospitalized; another (120 mg) was hospitalized, underwent gastric
lavage and remained normotensive; the third (105 mg) was hospitalized and had hypotension (90/50
mmHg) which normalized following plasma expansion. A case of accidental drug overdose has been
documented in a 19-month-old male who ingested 30 mg amlodipine (about 2 mg/kg). During the
emergency room presentation, vital signs were stable with no evidence of hypotension, but a heart
rate of 180 bpm. Ipecac was administered 3.5 hours after ingestion and on subsequent observation
(overnight) no sequelae were noted.
If massive overdose should occur, active cardiac and respiratory monitoring should be instituted.
Frequent blood pressure measurements are essential. Should hypotension occur, cardiovascular
support including elevation of the extremities and the judicious administration of fluids should be
initiated. If hypotension remains unresponsive to these conservative measures, administration of
vasopressors (such as phenylephrine) should be considered with attention to circulating volume and
urine output.
Intravenous calcium gluconate may help to reverse the effects of calcium entry blockade. As
amlodipine besylate is highly protein bound, hemodialysis is not likely to be of benefit.

DOSAGE AND ADMINISTRATION
Adults: The usual initial antihypertensive oral dose of amlodipine besylate is 5 mg once daily with
a maximum dose of 10 mg once daily. Small, fragile, or elderly individuals, or patients with hepatic
insufficiency may be started on 2.5 mg once daily and this dose may be used when adding
amlodipine besylate to other antihypertensive therapy.
Dosage should be adjusted according to each patient’s need. In general, titration should proceed
over 7 to 14 days so that the physician can fully assess the patient’s response to each dose level.
Titration may proceed more rapidly, however, if clinically warranted, provided the patient is assessed
frequently.
The recommended dose for chronic stable or vasospastic angina is 5 to 10 mg, with the lower dose
suggested in the elderly and in patients with hepatic insufficiency. Most patients will require 10 mg
for adequate effect. See ADVERSE REACTIONS section for information related to dosage and side
effects.
The recommended dose range for patients with coronary artery disease is 5 to 10 mg once daily. In
clinical studies the majority of patients required 10 mg (see CLINICAL PHARMACOLOGY, Clinical
studies).
Children: The effective antihypertensive oral dose in pediatric patients ages 6-17 years is 2.5 mg to
5 mg once daily. Doses in excess of 5 mg daily have not been studied in pediatric patients. See
CLINICAL PHARMACOLOGY.
Co-administration with Other Antihypertensive and/or Antianginal Drugs: Amlodipine besylate
has been safely administered with thiazides, ACE inhibitors, beta-blockers, long-acting nitrates,
and/or sublingual nitroglycerin.

HOW SUPPLIED
Amlodipine besylate 2.5 mg Tablets (amlodipine besylate, USP equivalent to 2.5 mg of amlodipine
per tablet) are supplied as white, round, flat-faced, beveled edged tablets debossed with IG on one
side and 237 on the other and supplied as follows:
NDC 31722-237-90 Bottle of 90
NDC 31722-237-10 Bottle of 1000
Amlodipine besylate 5 mg Tablets (amlodipine besylate, USP equivalent to 5 mg of amlodipine per
tablet) are supplied as white, round, flat-faced, beveled edged tablets debossed with IG on one side
and 238 on the other and supplied as follows:
NDC 31722-238-90 Bottle of 90
NDC 31722-238-10 Bottle of 1000
Amlodipine besylate 10 mg Tablets (amlodipine besylate, USP equivalent to 10 mg of amlodipine per
tablet) are supplied as white, round, flat-faced, beveled edged tablets debossed with IG on one side
and 239 on the other and supplied as follows:
NDC 31722-239-90 Bottle of 90
NDC 31722-239-10 Bottle of 1000
Manufactured by:
InvaGen Pharmaceuticals, Inc
Hauppauge, NY 11788
Manufactured for:
Camber Pharmaceuticals, Inc.
Piscataway, NJ 08854
Rev : 09/07

STORAGE AND HANDLING

Store at 20°-25°C (68°-77°F). [See USP Controlled Room Temperature].

Hypertensa™ PRODUCT INFORMATION Hypertensa (U.S. patent pending) capsules by oral administration. A specially formulated Medical Food product, consisting of a proprietary blend of amino acids and polyphenol ingredients in specific proportions, for the dietary management of the metabolic processes associated with hypertension (HT). Must be administered under physician supervision. Medical Foods Medical Food products are often used in hospitals (e.g., for burn victims or kidney dialysis patients) and outside of a hospital setting under a physician’s care (e.g., for PKU, AIDS patients, cardiovascular disease, sleep disorders) for the dietary management of diseases in patients with particular medical or metabolic needs due to their disease or condition. Congress defined "Medical Food" in the Orphan Drug Act and Amendments of 1988 as "a system which is formulated to be consumed or administered enterally [or orally] under the supervision of a physician and which is intended for the specific dietary management f a disease or condition for which distinctive nutritional requirements, based on recognized scientific principles, are established by medical evaluation." Medical Foods are complex formulated products, requiring sophisticated and exacting technology. Hypertensa has been developed, manufactured, and labeled in accordance with both the statutory and the FDA regulatory definition of a Medical Food. Hypertensa must be used while the patient is under the ongoing care of a physician. HYPERTENSION (HT) HT as a Metabolic Deficiency Disease A critical component of the definition of a Medical Food is the requirement for a distinctive nutritional deficiency. FDA scientists have proposed a physiologic definition of a distinctive nutritional deficiency as follows: “the dietary management of patients with specific diseases requires, in some instances, the ability to meet nutritional requirements that differ substantially from the needs of healthy persons. For example, in establishing the recommended dietary allowances f r general, healthy population, the Food and Nutrition Board of the Institute of Medicine National Academy of Sciences, recognized that different or distinctive physiologic requirements may exist for certain persons with "special nutritional needs arising from metabolic disorders, chronic diseases, injuries, premature birth, other medical conditions and drug therapies. Thus, the distinctive nutritional needs associated with a disease reflect the total amount needed by a healthy person to support life or maintain homeostasis, adjusted for the distinctive changes in the nutritional needs of the patient as a result of the effects of the disease process on absorption, metabolism and excretion.” It was also proposed that in patients with certain disease states who respond to nutritional therapies, a physiologic deficiency of the nutrient is assumed to exist. For example, if a patient with hypertension responds to an arginine formulation by decreasing the blood pressure, a deficiency of arginine is assumed to exist. Patients with hypertension are known to have nutritional deficiencies of arginine, choline, flavonoids, and certain antioxidants. Patients with hypertension frequently exhibit reduced plasma levels of arginine and have been shown to respond to oral administration of an arginine formulation. Research has shown that arginine reduced diets result in a fall of circulating arginine. Patients with hypertension have activation of the arginase pathway that diverts arginine from the production of nitric oxide to production of deleterious nitrogen molecules such as peroxynitrite leading to a reduced level of production of nitric oxide for a given arginine blood level. Research has also shown that a genetic predisposition can lead to increased arginine requirements in certain patients with hypertension. Arginine is required to fully potentiate nitric oxide synthesis by the arterioles. A deficiency of arginine leads to reduced nitric oxide production by the arterioles. Low fat diets, frequently used by patients with hypertension, are usually arginine deficient. Flavonoids potentiate the production of nitric oxide by the arterioles thereby reducing blood pressure in hypertensive patients. Low fat diets and diets deficient in flavonoid rich foods result in inadequate arginine and flavonoid concentrations, impeding nitric oxide production in certain patients with hypertension. Provision of arginine, choline, and flavonoids with antioxidants, in the correct proportions can restore the production of beneficial nitric oxide, thereby reducing blood pressure.

DESCRIPTION

PRODUCT DESCRIPTION Primary Ingredients Hypertensa consists of a proprietary blend of amino acids, cocoa, cinnamon and flavonoids in specific proportions. These ingredients fall into the category of Generally Regarded as Safe” (GRAS) as defined by the Food and Drug Administration (FDA) (Sections 201(s) and 409 of the Federal Food, Drug, and Cosmetic Act). A GRAS substance is distinguished from a food additive on the basis of the common knowledge about the safety of the substance for its intended use. The standard for an ingredient to achieve GRAS status requires not only technical demonstration of non-toxicity and safety, but also general recognition of safety through widespread usage and agreement of that safety by experts in the field. Many ingredients have been determined by the U.S. Food and Drug Administration (FDA) to be GRAS, and are listed as such by regulation, in Volume 21 Code of Federal Regulations (CFR) Sections 182, 184, and 186. Amino Acids Amino Acids are the building blocks of proteins. All amino acids are GRAS listed as they have been ingested by humans for thousands of years. The doses of the amino acids in Hypertensa are equivalent to those found in the usual human diet. Patients with hypertension may require an increased amount of certain amino acids that cannot be obtained from normal diet alone. Arginine, for example, is a conditional amino acid. The body can make arginine in the liver, but the liver produced arginine can only be used in the liver itself. Arginine is needed to produce nitric oxide (NO). NO is required to dilate the constricted blood vessels that are the cause of high blood pressure. Patients with hypertension have an increase in the enzyme, arginase that degrades arginine before it can be used to produce NO. Some patients with hypertension have a resistance to the use of arginine that is similar to the mechanism found in insulin resistance that is genetically determined. Patients with hypertension cannot acquire sufficient arginine from the diet without ingesting a prohibitively large amount of calories, particularly calories from protein. . Flavonoids Flavonoids are a group of phytochemical compounds found in all vascular plants including fruits and vegetables. They are a part of a larger class of compounds known as polyphenols. Many of the therapeutic or health benefits of colored fruits and vegetables, cocoa, red wine, and green tea are directly related to their flavonoid content. The specially formulated flavonoids found in Hypertensa cannot be obtained from conventional foods in the necessary proportions to elicit a therapeutic response. Other Ingredients Hypertensa contains the following “inactive” or other ingredients, as fillers, excipients, and colorings: magnesium stearate, microcrystalline cellulose, Maltodextrin NF, gelatin (as the capsule material), Physical Description Hypertensa is a yellow to light brown powder. Hypertensa contains L-Glutamine, L-Histadine, L-Arginine, L-Leucine, L-Cysteine, Whey Protein Hydrolysate, Choline Bitartrate, Cinnamon, Caffeine, Cocoa, Ginseng, and Grape Extract.

CLINICAL PHARMACOLOGY

CLINICAL PHARMACOLOGY Mechanism of Action Hypertensa acts by restoring and maintaining the balance of NO in patients with hypertension. Metabolism The amino acids in Hypertensa are primarily absorbed by the stomach and small intestines. All cells metabolize the amino acids in Hypertensa. Circulating arginine and choline blood levels determine the production of NO and acetylcholine. Excretion Hypertensa is not an inhibitor of cytochrome P450 1A2, 2C9, 2C19, 2D6, or 3A4. These isoenzymes are principally responsible for 95% of all detoxification of drugs, with CYP3A4 being responsible for detoxification of roughly 50% of drugs. Amino acids do not appear to have an effect on drug metabolizing enzymes.

INDICATIONS AND USAGE

INDICATIONS FOR USE Hypertensa is intended for the clinical dietary management of the metabolic processes in patients with hypertension.

CLINICAL STUDIES

CLINICAL EXPERIENCE Administration of Hypertensa has demonstrated significant functional improvements in blood pressure when used for the dietary management of the metabolic processes associated with hypertension. Administration of Hypertensa results in the reduction of blood pressure in hypertensive patients. Hypertensa has no effect on normal blood pressure.

CONTRAINDICATIONS

PRECAUTIONS AND CONTRAINDICATIONS Hypertensa is contraindicated in an extremely small number of patients with hypersensitivity to any of the nutritional components of Hypertensa.

ADVERSE REACTIONS

ADVERSE REACTIONS Oral supplementation with L-arginine at high doses up to 15 grams daily is generally well tolerated. The most commonly reported adverse reactions at higher doses — from 15 to 30 grams daily — are nausea, abdominal cramps, and diarrhea. Some patients may experience these symptoms at lower doses. The total combined amount of amino acids in each Hypertensa capsule does not exceed 400 mg.

DRUG INTERACTIONS

DRUG INTERACTIONS Hypertensa does not directly influence the pharmacokinetics of prescription drugs. Clinical experience has shown that administration of Hypertensa may allow for lowering the dose of co-administered drugs under physician supervision. POST-MARKETING SURVEILLANCE Post-marketing surveillance has shown no serious adverse reactions. Reported cases of mild rash and itching may have been associated with allergies to Hypertensa flavonoid ingredients, including cocoa and chocolate. The reactions were transient in nature and subsided within 24 hours.

OVERDOSAGE

OVERDOSE There is a negligible risk of overdose with Hypertensa as the total dosage of amino acids in a one month supply (90 capsules) is less than 36 grams. Overdose symptoms may include diarrhea, weakness, and nausea.

DOSAGE AND ADMINISTRATION Recommended Administration For the dietary management of the metabolic processes associated with hypertension. Take (2) capsules once or twice daily, as directed by physician. As with most amino acid formulations Hypertensa should be taken without food to increase the absorption of key ingredients.

HOW SUPPLIED

How Supplied Hypertensa is supplied in green and white, size 0 capsules in bottles of 60 and 90 capsules. Physician Supervision Hypertensa is a Medical Food product available by prescription only, and must be used while the patient is under ongoing physician supervision. U.S. patent pending. Manufactured by Arizona Nutritional Supplements, Inc. Chandler AZ 85225 Distributed by Physician Therapeutics LLC, Los Angeles, CA 90077. www.ptlcentral.com © Copyright 2003-2006, Physician Therapeutics LLC, all rights reserved NDC: 68405-1007-02 NDC: 68405-1007-03

STORAGE AND HANDLING

Storage Store at room temperature, 59-86OF (15-30OC) Protect from light and moisture. Hypertensa is supplied to physicians in a recyclable plastic bottle with a child-resistant cap.

PACKAGE LABEL

PHYSICIAN THERAPEUTICS HYPERTENSA Medical Food Rx only 90 Capsules Directions for use: Must be administered under physician supervision. For adults only. As a Medical Food, take two (2) capsules four times daily in between meals or as directed by physician. For the dietary management of hypertension. Contains no added sugar, starch, wheat, yeast, preservatives, artifical flavor. Storage: Keep tightly closed in a cool dry place 8-320 C (45-900F), relative humidity, below 50%. Warning: Keep this product out of the reach of children. NDC# 68405-1007-03 Ingredients: Each serving (per 2 capsules) contains: Proprietary Amino Acid Blend L-Glutamine L-Histadine, L-Arginine, L-Leucine, L-Cysteine, Whey Protein Hydrolysate, Choline Bitatarate, Cinnamon (bark), Caffeine, Cocoa(6% Theobromine) (fruit), Ginseng, Grape Extract (20% Polyphenol) (seed) other indgredients: Tricalcium phosphate, gelatin, silicon dioxide, vegetable magnesium stearate, microcrystalline cellulose, chlorophyllin copper complex, titanium dioxide. Distributed exclusive by: A Division of Targeted Medical Pharma, Inc Los Angeles, CA 90077 www.ptlcentral.com Patent Pending.

PACKAGE LABEL

For the Dietary Management of Hypertension. Two capsules twice daily or as directed by physician. See product label and insert. Hypertensa Medical Food PHYSICIAN THERAPEUTICS Hypertensa + Amlodipine 2.5 mg A Convenience Packed Medical Food and Drug Hypertenipine-2.5 PHYSICIAN THERAPEUTICS > Hypertensa 90 Capsuled > Amlodipine 2.5 mg 30 Tablets No Refills Without Physician Authorization Rx Only NDC# 68405-037-36 of this co-pack As prescribed by physician. See product label and product information insert. Amlodipine 2.5 mg Rx Drug